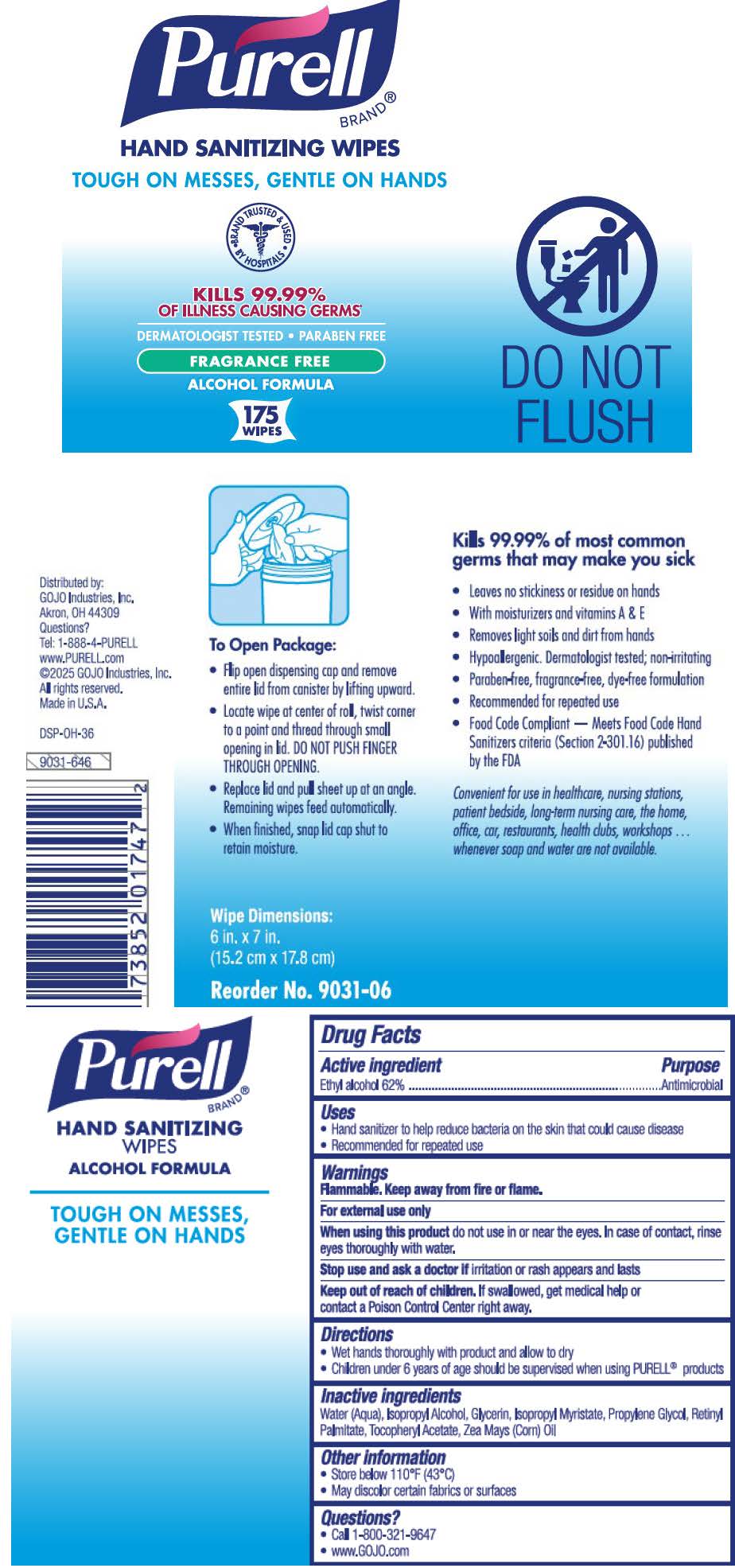 DRUG LABEL: PURELL Hand Sanitizing Wipes Alcohol Formula
NDC: 21749-367 | Form: CLOTH
Manufacturer: GOJO Industries, Inc.
Category: otc | Type: HUMAN OTC DRUG LABEL
Date: 20251106

ACTIVE INGREDIENTS: ALCOHOL 62 mL/100 mL
INACTIVE INGREDIENTS: WATER; ISOPROPYL ALCOHOL; GLYCERIN; ISOPROPYL MYRISTATE; PROPYLENE GLYCOL; VITAMIN A PALMITATE; .ALPHA.-TOCOPHEROL ACETATE; CORN OIL

PURELL Hand Sanitizing Wipes Alcohol Formula

Active ingredient

Ethyl alcohol 62%

Purpose

Antimicrobial

Use

Hand sanitizer to help reduce bacteria on the skin

Warnings

Flammable. Keep away from fire or flame. For external use only

When using this product do not use in or near the eyes. In case of contact, rinse eyes thoroughly with water.

Stop use and ask a doctor if irritation or rash appears and lasts

Keep out of reach of children. If swallowed, get medical help or contact a Poison Control Center right away.

Directions

• Wet hands thoroughly with product and allow to dry

• Children under 6 years of age should be supervised when using PURELL® products

Other information

• Store below 110°F (43°C)

• May discolor certain fabrics or surfaces

Inactive ingredients

Water (Aqua), Isopropyl Alcohol, Glycerin, Isopropyl Myristate, Propylene Glycol, Retinyl Palmitate, Tocopheryl Acetate, Zea Mays (Corn) Oil